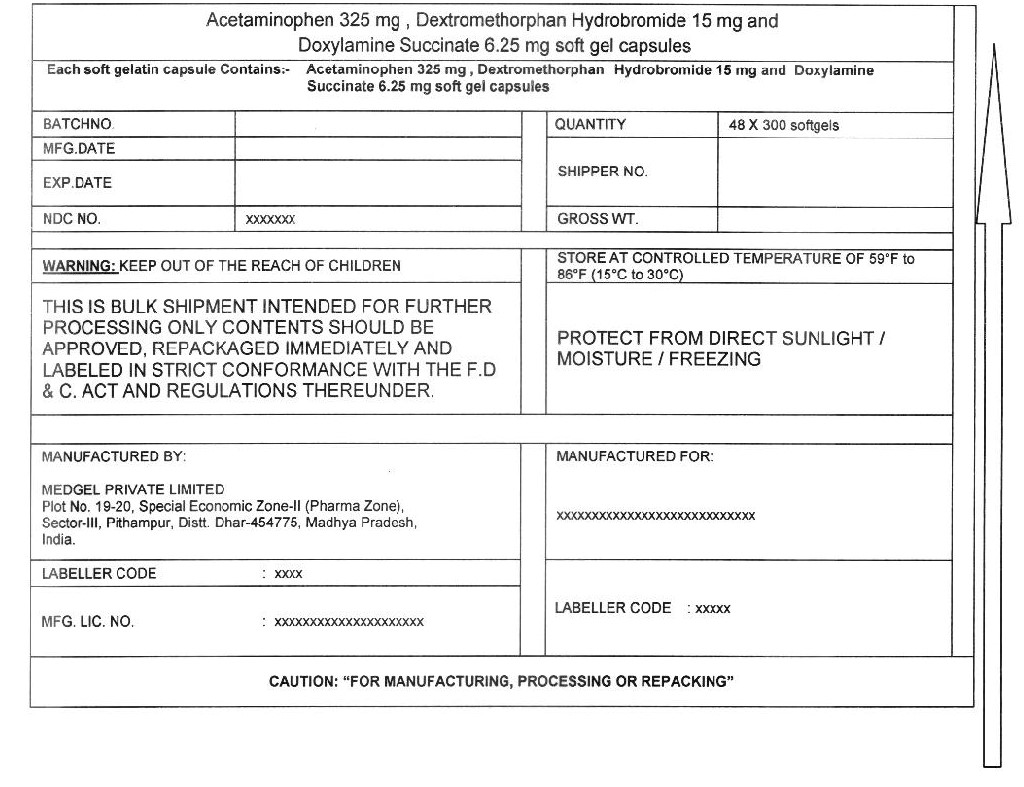 DRUG LABEL: acetaminophen, dextromethorphan hydrobromide, doxylamine succinate
NDC: 55629-014 | Form: CAPSULE, LIQUID FILLED
Manufacturer: ONE2ZEE LIMITED LIABILITY COMPANY
Category: otc | Type: HUMAN OTC DRUG LABEL
Date: 20230325

ACTIVE INGREDIENTS: ACETAMINOPHEN 325 mg/1 1; DEXTROMETHORPHAN HYDROBROMIDE 15 mg/1 1; DOXYLAMINE SUCCINATE 6.25 mg/1 1
INACTIVE INGREDIENTS: POLYETHYLENE GLYCOL 400; PROPYLENE GLYCOL; POVIDONE K30; FD&C BLUE NO. 1; D&C YELLOW NO. 10; TITANIUM DIOXIDE; GELATIN; GLYCERIN; SORBITOL; WATER

NIGHTTIME COLD AND FLU capsule, liquid filled (Acetaminophen 325mg, Dextromethorpha HBr 15mg and Doxylamine Succinate 6.25mg)

Active ingredients (in each capsule)

Acetaminophen 325 mg

Dextromethorphan HBr 15 mg

Doxylamine Succinate 6.25 mg

Purpose:

Pain reliever/ fever reducer

Cough suppressant

Antihistamine

Uses:

temporarily relieves common cold/flu symptoms:

- cough due to minor throat & bronchial irritation
- sore throat
- headache
- minor aches/pains
- fever
- runny nose & sneezing

Warnings:

Liver warning This product contains acetaminophen. Severe liver damage may occur if you take:

- more than 4 doses in 24 hours, which is the maximum daily amount for this product
- with other drugs containing acetaminophen
- 3 or more alcoholic drinks daily while using this product

Sore throat warning If sore throat is severe, lasts more than 2 days, occurs with or is followed by fever, headache, rash, nausea, or vomiting, see a doctor promptly.

Do not use

- with any other drug containing acetaminophen (prescription or nonprescription). If you are not sure whether a drug contains acetaminophen, ask a doctor or pharmacist.
- if you are now taking a prescription monoamine oxidase inhibitor (MAOI) (certain drugs for depression, psychiatric, or emotional conditions, or Parkinson's disease), or for 2 weeks after stopping the MAOI drug. If you do not know if your prescription drug contains an MAOI, ask a doctor or pharmacist before taking this product.
- To make a child sleep

Ask a doctor before use if you have

- liver disease
- glaucoma
- cough that occurs with too much phlegm (mucus)
- a breathing problem or chronic cough that lasts or as occurs with smoking, asthma, chronic bronchitis or emphysema
- trouble urinating due to enlarged prostate gland

When using this product

do not use more than directed
excitability may occur, especially in children
marked drowsiness may occur
avoid alcoholic drinks
be careful when driving a motor vehicle or operating machinery
alcohol, sedatives, and tranquilizers may increase drowsiness

Stop use and ask a doctor if

- pain or cough gets worse or lasts more than 7 days
- fever gets worse or lasts more than 3 days
- redness or swelling is present
- new symptoms occur
- cough comes back or occurs with rash or headache that lasts. These could be signs of a serious condition.

Directions

- take only as directed - see Overdose warning
- do not exceed 4 doses per 24 hours

Adults and children 12 years of age and older | 2 LiquiCaps with water every 4 hours
Children under 12 years of age | ask doctor

When using other Nighttime or Daytime products, carefully read each label to ensure correct dosing.

Other Information

- store at room temperature 59°-86°F (15°-30°C)

Inactive ingredients

polyethylene glycol 400, propylene glycol, povidone k30, fd&c blue no. 1, d&c yellow no. 10, titanium dioxide, gelatin, glycerin, sorbitol, water

PRINCIPAL DISPLAY PANEL - Shipping Label

Acetaminophen, Dextromethorphan HBr, Doxylamine Succinate capsules

Each Softgel Contains:
(Acetaminophen USP 325 mg, Dextromethorphan Hydrobromide USP 15 mg, Doxylamine Succinate 6.25 mg)

LOT NO:
DRUM NO:
MFG DATE:
QUANTITY:
NDC NO: 55629-014-
EXP DATE:

WARNING:
KEEP OUT OF REACH OF CHILDREN

STORE CONTROLLED ROOM TEMPERATURE OF 59° - 86°F (15° - 30°C)
PROTECT FROM LIGHT, MOISTURE AND FREEZING

THIS IS A BULK SHIPMENT INTENDED FOR FURTHER PROCESSING ONLY.

CONTENTS SHOULD BE APPROVED, REPACKAGED IMMEDIATELY AND LABELED IN STRICT CONFORMANCE WITH
THE F.D & C.ACT AND REGULATIONS THEREUNDER.